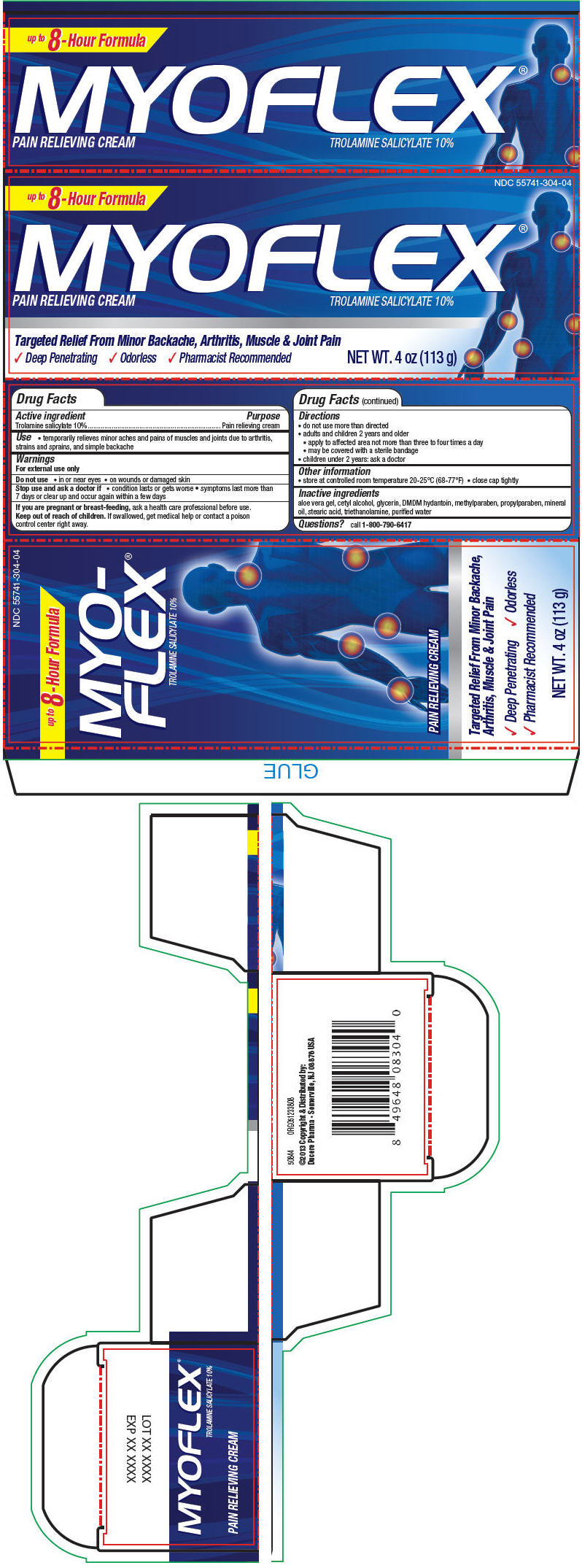 DRUG LABEL: Myoflex
NDC: 55741-304 | Form: CREAM
Manufacturer: Dr. Reddy's Laboratories Inc.
Category: otc | Type: HUMAN OTC DRUG LABEL
Date: 20160615

ACTIVE INGREDIENTS: Trolamine salicylate 10 g/100 g
INACTIVE INGREDIENTS: aloe vera leaf; cetyl alcohol; glycerin; DMDM hydantoin; methylparaben; propylparaben; mineral oil; stearic acid; trolamine; water

Myoflex®

Drug Facts

Active ingredient

Trolamine salicylate 10%

Purpose

Pain relieving cream

Use

- temporarily relieves minor aches and pains of muscles and joints due to arthritis, strains and sprains, and simple backache

Warnings

For external use only

Do not use

- in or near eyes
- on wounds or damaged skin

Stop use and ask a doctor if

- condition lasts or gets worse
- symptoms last more than 7 days or clear up and occur again within a few days

PREGNANCY OR BREAST FEEDING

If you are pregnant or breast-feeding, ask a health care professional before use.

Keep out of reach of children. If swallowed, get medical help or contact a poison control center right away.

Directions

- do not use more than directed
- adults and children 2 years and older
  - apply to affected area not more than three to four times a day
  - may be covered with a sterile bandage
- children under 2 years: ask a doctor

Other information

- store at controlled room temperature 20-25°C (68-77°F)
- close cap tightly

Inactive ingredients

aloe vera gel, cetyl alcohol, glycerin, DMDM hydantoin, methylparaben, propylparaben, mineral oil, stearic acid, triethanolamine, purified water

Questions?

call 1-800-790-6417

PRINCIPAL DISPLAY PANEL - 113 g Tube Box

NDC 55741-304-04

up to 8 - Hour Formula

MYOFLEX®
PAIN RELIEVING CREAM

TROLAMINE SALICYLATE 10%

Targeted Relief From Minor Backache, Arthritis, Muscle & Joint Pain

✓ Deep Penetrating ✓ Odorless ✓ Pharmacist Recommended

NET WT. 4 oz (113 g)